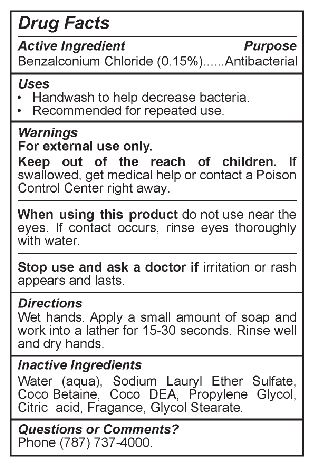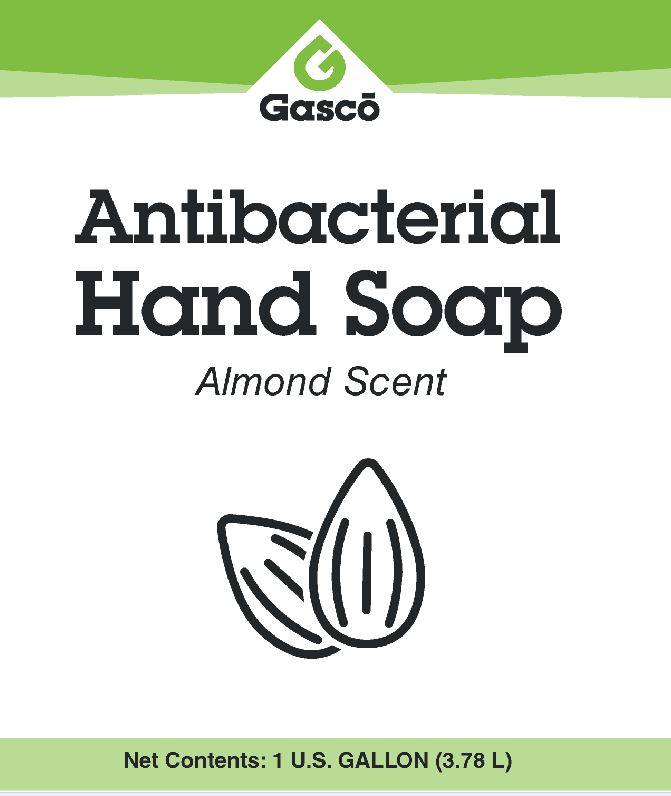 DRUG LABEL: GASCO ANTIBACTERIAL
NDC: 70185-800 | Form: SOAP
Manufacturer: GASCO INDUSTRIAL CORP
Category: otc | Type: HUMAN OTC DRUG LABEL
Date: 20251014

ACTIVE INGREDIENTS: BENZALKONIUM CHLORIDE 1.5 mg/1 mL
INACTIVE INGREDIENTS: SODIUM LAURETH SULFATE; N-NONYLPHENOL (MIXED ISOMERS); COCO DIETHANOLAMIDE; BENZALDEHYDE; SODIUM CHLORIDE; COCAMIDOPROPYL BETAINE

Active ingredient
Benzalkonium chloride 0.15%

PURPOSE

Antibacterial

Stop use and ask a doctor if irritation or rash appears and lasts.

Stop use and ask a doctor if irritation or rash appears and lasts.

KEEP OUT OF REACH OF CHILDREN

Keep out of the reach of children. If swallowed, get medical help or contact a Poison Control Center right away.

Do not use near the eyes. If contact occurs, rinse eyes thoroughly with water.

INDICATIONS AND USAGE

• Handwash to help decrease bacteria.
• Recommended for repeated use.

DOSAGE AND ADMINISTRATION

Wet hands. Apply a small amount of soap and work into a lather for 15–30 seconds. Rinse well and dry hands.

WARNINGS

For external use only.
Keep out of the reach of children. If swallowed, get medical help or contact a Poison Control Center right away.
When using this product do not use near the eyes. If contact occurs, rinse eyes thoroughly with water.
Stop use and ask a doctor if irritation or rash appears and lasts.

INACTIVE INGREDIENT

Water (aqua), Sodium Laureth Sulfate, Coco Betaine, Coco DEA, Propylene Glycol, Citric acid, Fragrance, Glycol Stearate.